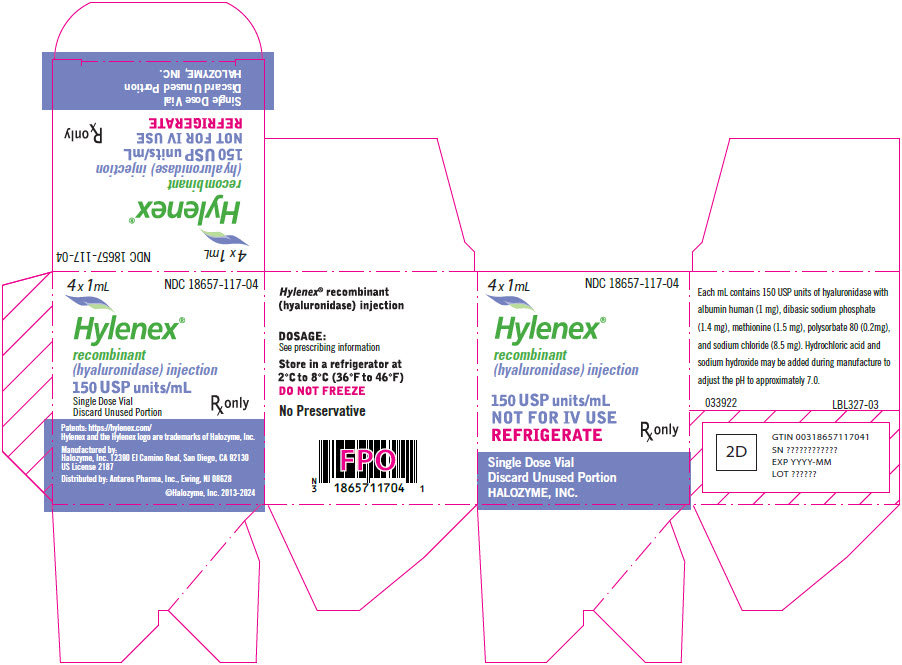 DRUG LABEL: HYLENEX Recombinant
NDC: 18657-117 | Form: INJECTION, SOLUTION
Manufacturer: Antares Pharma, Inc.
Category: prescription | Type: HUMAN PRESCRIPTION DRUG LABEL
Date: 20241111

ACTIVE INGREDIENTS: Hyaluronidase (Human Recombinant) 150 [USP'U]/1 mL
INACTIVE INGREDIENTS: sodium chloride 8.5 mg/1 mL; SODIUM PHOSPHATE, DIBASIC, UNSPECIFIED FORM 1.4 mg/1 mL; albumin human 1 mg/1 mL; Methionine 1.5 mg/1 mL; polysorbate 80 0.2 mg/1 mL; hydrochloric acid; sodium hydroxide

HIGHLIGHTS OF PRESCRIBING INFORMATION

These highlights do not include all the information needed to use HYLENEX recombinant safely and effectively. See full prescribing information for HYLENEX recombinant.
HYLENEX recombinant (hyaluronidase) injection for infiltration use, for interstitial use, for intramuscular use, for intraocular use, for peribulbar use, retrobulbar use, for soft tissue use or for subcutaneous use
Initial U.S. Approval: 2005

1. Indications and Usage

HYLENEX recombinant is an endoglycosidase indicated as an adjuvant

- in subcutaneous fluid administration for achieving hydration (1.1)
- to increase the dispersion and absorption of other injected drugs (1.2)
- in subcutaneous urography for improving resorption of radiopaque agents (1.3)

2. Dosage and administration

- See Full Prescribing Information for all approved routes of administration. (2.1)
- Subcutaneous Fluid Administration: Inject 150 USP units HYLENEX recombinant prior to subcutaneous fluid administration. It will facilitate absorption of 1,000 mL or more of solution. The dosage of subcutaneous fluids administered is dependent upon the age, weight, and clinical condition of the patient as well as laboratory determinations. The rate and volume of subcutaneous fluid administration should not exceed those employed for intravenous infusion. (2.2)
- Increasing Dispersion and Absorption of Injected or Subcutaneously Infused Drugs: Inject 50 units to 300 units (most typically 150 USP units) HYLENEX recombinant prior to drug administration. Alternatively, add 50 units to 300 units (most typically 150 USP units) HYLENEX recombinant to the injection solution. (2.3)
- Subcutaneous Urography: Inject 75 USP units HYLENEX recombinant subcutaneously over each scapula, followed by injection of the contrast medium at the same sites. (2.4)

3. Dosage Forms and Strengths

- Injection: 150 USP units/mL solution in a single-dose vial. (3)

4. Contraindications

- Hypersensitivity (4)

5. Warnings and Precautions

- Spread of Localized Infection (5.1)
- Ocular Damage (5.2)

6. Adverse Reactions

- Allergic and anaphylactic-like reactions have been reported, rarely. (6)

To report SUSPECTED ADVERSE REACTIONS, contact Halozyme,ºInc. at 1-877-877-1679 or FDA at 1-800-FDA-1088 or www.fda.gov/medwatch.

7. Drug Interactions

- Furosemide, the benzodiazepines and phenytoin are incompatible with hyaluronidase. (7.1)
- Hyaluronidase should not be used to enhance the dispersion and absorption of dopamine and/or alpha agonist drugs. (7.2)
- Local anesthetics: Hyaluronidase hastens onset and shortens duration of effect, increases incidence of systemic reactions. (7.3)
- Large doses of salicylates, cortisone, ACTH, estrogens or antihistamines may require larger amounts of hyaluronidase for equivalent dispersing effect. (7.4)

8. Use in Specific Populations

- Pediatric Use: The dosage of subcutaneous fluids administered is dependent upon the age, weight, and clinical condition of the patient. For premature infants or during the neonatal period, the daily dosage should not exceed 25 mL/kg of body weight, and the rate of administration should not be greater than 2 mL per minute. Special care must be taken in pediatric patients to avoid over hydration by controlling the rate and total volume of the infusion. (2.2, 8.4, 14)

FULL PRESCRIBING INFORMATION

1. Indications and Usage

1.1. Subcutaneous Fluid Administration

HYLENEX recombinant is indicated as an adjuvant in subcutaneous fluid administration for achieving hydration.

1.2. Dispersion and Absorption of Injected Drugs

HYLENEX recombinant is indicated as an adjuvant to increase the dispersion and absorption of other injected drugs.

1.3. Subcutaneous Urography

HYLENEX recombinant is indicated as an adjunct in subcutaneous urography for improving resorption of radiopaque agents.

2. Dosage and administration

2.1. Important Administration Instructions

HYLENEX recombinant should not be administered intravenously. Its effects relative to dispersion and absorption of other drugs are not produced when it is administered intravenously because the enzyme is rapidly inactivated.

HYLENEX recombinant may be administered for infiltration use, interstitial use, intramuscular use, intraocular use, peribulbar use, retrobulbar use, soft tissue use or subcutaneous use. Visually inspect parenteral drug products for particulate matter and discoloration prior to administration.

2.2. Subcutaneous Fluid Administration

Lightly pinch the skin up into a small mound and insert the needle/catheter into the subcutaneous space. Inject 150 USP units of HYLENEX recombinant prior to start of subcutaneous fluid administration to facilitate absorption of up to 1,000 mL or more of solution. Inject HYLENEX recombinant through the catheter hub or injection port closest to the needle/catheter. Begin administration of solution. Solution should start in readily. As with all parenteral fluid therapy, observe effect closely, with the same precautions for restoring fluid and electrolyte balance as in intravenous injections. The dose, the rate of injection, and the type of solution (saline, glucose, Ringer's, etc.) must be adjusted carefully to the individual patient. When solutions devoid of inorganic electrolytes are administered subcutaneously, hypovolemia may occur. This may be prevented by using solutions containing adequate amounts of inorganic electrolytes and/or controlling the volume and speed of administration.

HYLENEX recombinant may be added to small volumes of solution, such as fluid replacement solutions or solutions of drugs for subcutaneous injection. Subcutaneous fluids should be administered as directed by a physician. The dosage of subcutaneous fluids administered is dependent upon the age, weight, and clinical condition of the patient as well as laboratory determinations. The rate and volume of subcutaneous fluid administration should not exceed those employed for intravenous infusion. For premature infants or during the neonatal period, the daily dosage should not exceed 25 mL/kg and the rate of administration should not be greater than 2 mL per minute.

2.3. Dispersion and Absorption of Injected Drugs

Hylenex can be used to enhance the dispersion and absorption of other injected or subcutaneously infused drugs by pre-administration of HYLENEX recombinant or by adding 50 units to 300 units, most typically 150 USP units hyaluronidase, to the injection solution prior to infiltration use, interstitial use, intramuscular use, intraocular use, retrobulbar use, soft tissue use or subcutaneous use.

2.4. Subcutaneous Urography

The subcutaneous route of administration of urographic contrast media may be considered when intravenous administration cannot be successfully accomplished, particularly in infants and small children. With the patient prone, inject 75 USP units of HYLENEX recombinant subcutaneously over each scapula, followed by injection of the contrast medium at the same sites.

3. Dosage Forms and Strengths

Injection: 150 USP units/mL as a clear and colorless solution in a single-dose vial.

4. Contraindications

HYLENEX recombinant is contraindicated in patients with known hypersensitivity to hyaluronidase or any of the excipients in HYLENEX recombinant. Discontinue HYLENEX recombinant if sensitization occurs.

5. Warnings and Precautions

5.1. Spread of Localized Infection

Hyaluronidase should not be injected into or around an infected or acutely inflamed area because of the danger of spreading a localized infection.

Hyaluronidase should not be used to reduce the swelling of bites or stings.

5.2. Ocular Damage

Hyaluronidase should not be applied directly to the cornea. It is not for topical use.

6. Adverse Reactions

The following adverse reactions have been identified during post-approval use of hyaluronidase products. Because these reactions are reported voluntarily from a population of uncertain size, it is not always possible to reliably estimate their frequency or establish a causal relationship to drug exposure.

The most frequently reported adverse reactions have been mild local injection site reactions such as erythema and pain. Hyaluronidase has been reported to enhance the adverse reactions associated with co-administered drug products. Edema has been reported most frequently in association with subcutaneous fluid administration. Allergic reactions (urticaria or angioedema) have been reported in less than 0.1% of patients receiving hyaluronidase. Anaphylactic-like reactions following retrobulbar block or intravenous injections have occurred, rarely.

7. Drug Interactions

It is recommended that appropriate references be consulted regarding physical or chemical incompatibilities before adding HYLENEX recombinant to a solution containing another drug.

7.1. Incompatibilities

Furosemide, the benzodiazepines and phenytoin have been found to be incompatible with hyaluronidase.

Admixture stability studies have shown that 2% lidocaine with 1:100,000 or 1:200,000 epinephrine is incompatible with hyaluronidase due to the presence of sodium metabisulfite, a common additive in anesthetic products containing epinephrine.

7.2. Drug-Specific Precautions

Hyaluronidase should not be used to enhance the dispersion and absorption of dopamine and/or alpha agonist drugs.

When considering the administration of any other drug with hyaluronidase, it is recommended that appropriate references first be consulted to determine the usual precautions for the use of the other drug.

7.3. Local Anesthetics

When hyaluronidase is added to a local anesthetic agent, it hastens the onset of analgesia and tends to reduce the swelling caused by local infiltration, but the wider spread of the local anesthetic solution increases its absorption; this shortens its duration of action and tends to increase the incidence of systemic reaction.

7.4. Salicylates, Cortisone, ACTH, Estrogens and Antihistamines

Patients receiving large doses of salicylates, cortisone, ACTH, estrogens or antihistamines may require larger amounts of hyaluronidase for equivalent dispersing effect, since these drugs apparently render tissues partly resistant to the action of hyaluronidase.

8. Use in Specific Populations

8.1. Pregnancy

Risk Summary

There are no adequate and well-controlled studies of HYLENEX recombinant administration in pregnant women to inform a drug-associated risk. Subcutaneous administration of HYLENEX recombinant to pregnant mice throughout organogenesis did not produce teratogenic effects at clinically relevant doses. Administration of HYLENEX recombinant to mice in a pre-/postnatal study did not produce adverse effects on offspring at clinically relevant doses.

Human Data

Limited available data with HYLENEX recombinant in pregnant women have not identified any potential risks.

Animal Data

In an embryofetal development study, subcutaneous administration of hyaluronidase to pregnant mice throughout organogenesis produced reduced fetal weight and increased numbers of fetal resorptions at daily doses greater or equal to 3 mg/kg (approximately 360,000 USP units/kg). No malformations were produced at any dose up to approximately 18 mg/kg (approximately 2,200,000 USP units/kg). These doses are several orders of magnitude greater than the maximum recommended human dose (5 USP units/kg).

In a pre- and postnatal development study, mice were dosed daily by subcutaneous injection with hyaluronidase at dose levels up to 9 mg/kg (approximately 1,100,000 USP units/kg). The study found no adverse effects on sexual maturation, learning and memory of offspring, or their ability to produce another generation of offspring.

8.2. Lactation

Risk Summary

There is no information regarding the presence of HYLENEX recombinant in human milk, the effects on the breastfed infants, or the effects on milk production to inform risk of HYLENEX recombinant to an infant during lactation.

The developmental and health benefits of breastfeeding should be considered along with the mother's clinical need for HYLENEX recombinant.

8.4. Pediatric Use

Clinical hydration requirements for children can be achieved through administration of subcutaneous fluids facilitated with HYLENEX recombinant.

The dosage of subcutaneous fluids administered is dependent upon the age, weight, and clinical condition of the patient as well as laboratory determinations. The potential for chemical or physical incompatibilities should be kept in mind [see Drug Interactions (7)].

The rate and volume of subcutaneous fluid administration should not exceed those employed for intravenous infusion. For premature infants or during the neonatal period, the daily dosage should not exceed 25 mL/kg of body weight, and the rate of administration should not be greater than 2 mL per minute.

During subcutaneous fluid administration, special care must be taken in pediatric patients to avoid over hydration by controlling the rate and total volume of the infusion [see Dosage and Administration (2.1)].

8.5. Geriatric Use

No overall differences in safety or effectiveness have been observed between elderly and younger adult patients.

11 Description

Hyaluronidase is an endoglycosidase used to increase the dispersion and absorption of co-administered drugs when administered subcutaneously. It is a glycosylated single-chain protein produced by genetically engineered Chinese Hamster Ovary (CHO) cells containing a DNA plasmid encoding for a soluble fragment of human hyaluronidase (PH20). Hyaluronidase has an approximate molecular weight of 61 kDa.

HYLENEX recombinant (hyaluronidase) injection is supplied as a sterile, clear and colorless, nonpreserved, ready-for-use 1 mL solution in a single-dose vial for infiltration use, for interstitial use, for intramuscular use, for intraocular use, for peribulbar use, for retrobulbar use, for soft tissue use, or for subcutaneous use. Each mL contains 150 USP units of hyaluronidase with albumin human (1 mg), dibasic sodium phosphate (1.4 mg), methionine (1.5 mg), polysorbate 80 (0.2 mg), and sodium chloride (8.5 mg). Hydrochloric acid and sodium hydroxide may be added during manufacture to adjust the pH. HYLENEX has an approximate pH of 7.0.

12 Clinical Pharmacology

12.1 Mechanism of Action

Hyaluronidase is a dispersion agent, which modifies the permeability of connective tissue through the hydrolysis of hyaluronic acid, a polysaccharide found in the intercellular ground substance of connective tissue, and of certain specialized tissues, such as the umbilical cord and vitreous humor. Hyaluronic acid is also present in the capsules of type A and C hemolytic streptococci. Hyaluronidase hydrolyzes hyaluronic acid by splitting the glucosaminidic bond between C1 of an N-acetylglucosamine moiety and C4 of a glucuronic acid moiety. This temporarily decreases the viscosity of the cellular cement and promotes dispersion of injected fluids or of localized transudates or exudates, thus facilitating their absorption.

Hyaluronidase cleaves glycosidic bonds of hyaluronic acid and, to a variable degree, some other acid mucopolysaccharides of the connective tissue. The activity is measured in vitro by monitoring the decrease in the amount of an insoluble serum albumin-hyaluronic acid complex as the enzyme cleaves the hyaluronic acid component.

12.2 Pharmacodynamics

In the absence of hyaluronidase, material injected subcutaneously disperses very slowly. Hyaluronidase facilitates dispersion, provided local interstitial pressure is adequate to furnish the necessary mechanical impulse. Such an impulse is normally initiated by injected solutions. The rate and extent of dispersion and absorption is proportionate to the amount of hyaluronidase and the volume of solution.

The reconstitution of the dermal barrier removed by intradermal injection of hyaluronidase (20, 2, 0.2, 0.02, and 0.002 USP units/mL) to adult humans indicated that at 24 hours the restoration of the barrier is incomplete and inversely related to the dosage of hyaluronidase; at 48 hours, the barrier is completely restored in all treated areas.

Results from an experimental study, in humans, on the influence of hyaluronidase in bone repair support the conclusion that hyaluronidase alone, in the usual clinical dosage, does not deter bone healing.

12.3 Pharmacokinetics

Knowledge of the mechanisms involved in the disappearance of injected hyaluronidase is limited. It is known, however, that the components in blood of a number of mammalian species bring about the inactivation of hyaluronidase.

Studies have demonstrated that hyaluronidase is antigenic; repeated injections of relatively large amounts of hyaluronidase preparations may result in the formation of neutralizing antibodies.

13 Nonclinical Toxicology

13.1 Carcinogenesis, Mutagenesis, Impairment of Fertility

Long-term animal studies have not been performed to assess the carcinogenic or mutagenic potential of hyaluronidase. When hyaluronidase was subcutaneously administered to cynomolgus monkeys in a 39-week general toxicity study, no toxicity to the male or female reproductive systems was reported for measured parameters (i.e., semen analyses, hormone levels, menstrual cycles, gross pathology, histopathology, organ weight data), at dose levels up to 2 mg/kg (approximately 220,000 USP units/kg).

14 Clinical Studies

HYLENEX recombinant facilitated the administration of subcutaneous fluids in pediatric patients with mild to moderate dehydration in an open-label, multicenter, single arm study in fifty-one (51) patients. A subcutaneous injection of 1 mL (150 USP units) of HYLENEX recombinant was immediately followed by subcutaneous infusion of isotonic fluids in either the mid-anterior thigh or the inter-scapular area of the upper back.

The safety and flow rate of subcutaneously administered Lactated Ringer's (LR) solution with and without HYLENEX recombinant was evaluated in a prospective, randomized, double-blinded, placebo-controlled, within-subject, single-center study in fifty-four (54) healthy volunteers. The mean HYLENEX recombinant facilitated infusion rate was 464 mL/hr versus 118 mL/hr for the saline control (p < 0.001, paired t-test).

16 How Supplied/Storage and Handling

HYLENEX recombinant (hyaluronidase) injection is supplied sterile clear and colorless solution as 150 USP units of nonpreserved hyaluronidase per mL in a single-dose glass vial. Discard unused portion.

STORAGE AND HANDLING

HYLENEX recombinant is supplied in the following packaging:

1 mL single-dose vial (NDC 18657-117-01) available in boxes of 4 (NDC 18657-117-04)

Store unopened in a refrigerator at 2°C to 8°C (36°F to 46°F).

DO NOT FREEZE.

17 Patient Counseling Information

Important Precautions Regarding HYLENEX recombinant

Instruct patients that HYLENEX recombinant is being used to increase the dispersion and absorption of fluids or other injected drugs, as appropriate to the intended use.

Instruct patients that there may be mild local injection site signs and symptoms, such as redness, swelling, itching, or pain localized to the site of injection.

What Patients Should Know About Adverse Reactions

Advise patients that the most frequently reported adverse reactions have been mild local injection site reactions such as redness, swelling, itching, or pain.

Anaphylactic-like reactions, and allergic reactions, such as hives, have been reported rarely in patients receiving hyaluronidases.

Patients Should Inform Their Doctors If Taking Other Medications

Instruct patients that they may not receive furosemide, the benzodiazepines, phenytoin, dopamine and/or alpha agonists with HYLENEX recombinant. These medications have been found to be incompatible with hyaluronidase.

Advise patients that if they are taking salicylates (e.g., aspirin), steroids (e.g., cortisone or estrogens), or antihistamines, they may need to be prescribed larger amounts of hyaluronidase for equivalent dispersing effect.

Hylenex and the Hylenex logo are trademarks of Halozyme, Inc.

Patents: https://halozyme.com/

Manufactured by: Halozyme, Inc., San Diego, CA 92130
US license 2187
Distributed by: Antares Pharma, Inc. Ewing, NJ 08628

For Product Inquiry: 1 855 495-3639

Rev. 11/2024
LBL301-07

PRINCIPAL DISPLAY PANEL - 4 Vial Box Carton

4 x 1mL
NDC 18657-117-04

Hylenex®
recombinant
(hyaluronidase) injection

150 USP units/mL
NOT FOR IV USE
REFRIGERATE

Rx only

Single Dose Vial
Discard Unused Portion
HALOZYME, INC.